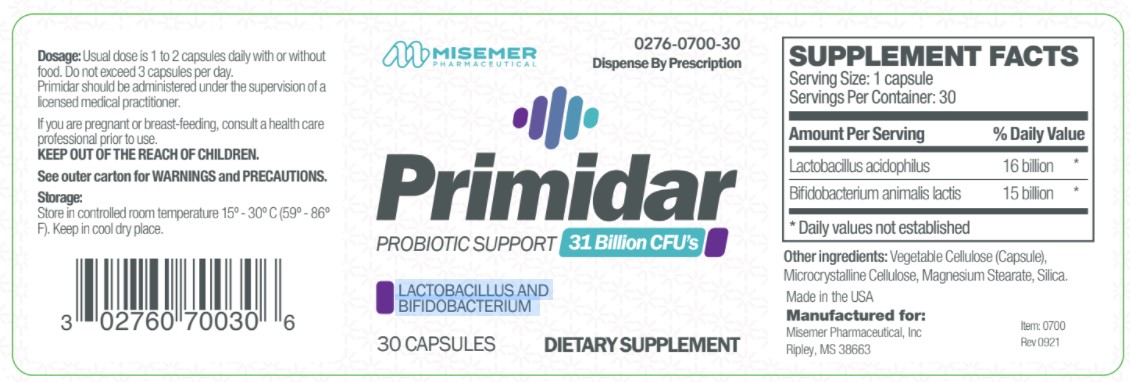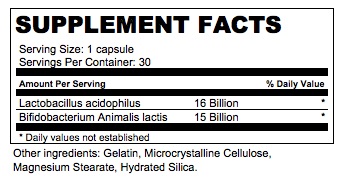 DRUG LABEL: Primidar
NDC: 0276-0700 | Form: CAPSULE
Manufacturer: Misemer Pharmaceuticals, Inc.
Category: other | Type: DIETARY SUPPLEMENT
Date: 20211101

ACTIVE INGREDIENTS: LACTOBACILLUS ACIDOPHILUS 16000000000 [CFU]/1 1; BIFIDOBACTERIUM ANIMALIS LACTIS 15000000000 [CFU]/1 1
INACTIVE INGREDIENTS: MICROCRYSTALLINE CELLULOSE; MAGNESIUM STEARATE; HYDRATED SILICA

Primidar
Dietary Supplement

DESCRIPTION

Primidar is an orally administered prescription probiotic formulation for the clinical dietary management of suboptimal nutritional status in patients where advanced supplementation is required and nutritional supplementation in physiologically stressful conditions for maintenance of good health is needed.

Primidar should be administered under the supervision of a licensed medical practitioner.

WARNINGS AND PRECAUTIONS

This product is contraindicated in patients with a known hypersensitivity to any of the ingredients.

Primidar should only be used under the direction and supervision of a licensed medical practitioner. Use with caution in patients that may have a medical condition, are pregnant, lactating, trying to conceive, under the age of 18, or taking medications.

DOSAGE AND ADMINISTRATION

Usual dose is 1 to 2 capsule daily with or without food. Do not exceed 3 capsules per day.

HOW SUPPLIED:

Primidar is supplied as clear vegetarian capsules dispensed in white HDPE plastic bottles of 30ct.
Item 0276-0700-30

STORAGE:

Store at controlled room temperature 15°-30°C (59°F-86°F). Keep in cool dry place. Call your doctor about side effects. You may report side effects to FDA at 1-800-FDA-1088.

KEEP THIS OUT OF THE REACH OF CHILDREN.

PACKAGE LABEL

Primidar is an orally administered prescription probiotic supplement, indicated for the distinct nutritional requirements
of patients in need of dietary supplementation as determined by a licensed medical practitioner. Primidar should be
administered under the supervision of a licensed medical practitioner.